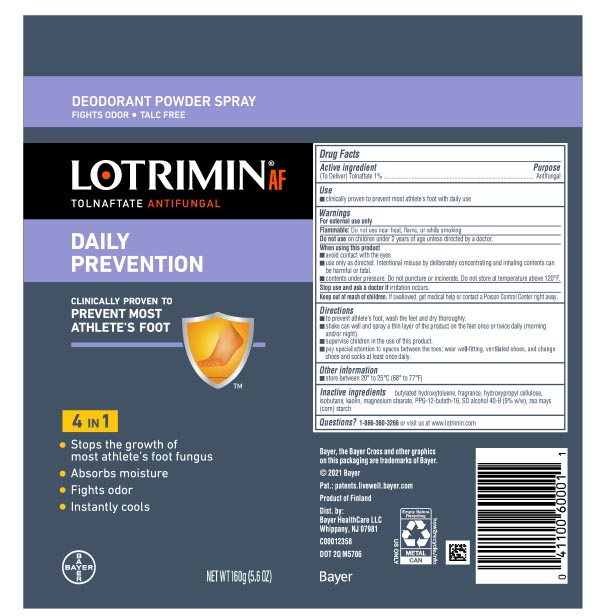 DRUG LABEL: Lotrimin
NDC: 11523-0136 | Form: AEROSOL, POWDER
Manufacturer: Bayer HealthCare LLC.
Category: otc | Type: HUMAN OTC DRUG LABEL
Date: 20251204

ACTIVE INGREDIENTS: TOLNAFTATE 10 mg/1 g
INACTIVE INGREDIENTS: MAGNESIUM STEARATE; STARCH, CORN; BUTYLATED HYDROXYTOLUENE; ALCOHOL; HYDROXYPROPYL CELLULOSE, UNSPECIFIED; PPG-12-BUTETH-16; ISOBUTANE; KAOLIN

Lotrimin Daily Prevention Powder Spray TALC FREE UI 1615422

Drug Facts

Active Ingredient

(To Deliver)Tolnaftate 1%

Purpose

Antifungal

Use

clinically proven to prevent most athlete’s foot with daily use

Warnings

For external use only

Flammable: Do not use near heat, flame, or while smoking

Do not use on children under 2 years of age unless directed by a doctor

When using this product

- avoid contact with the eyes
- use only as directed. Intentional misuse by deliberately concentrating and inhaling contents can be harmful or fatal.
- contents under pressure. Do not puncture or incinerate. Do not store at temperatures above 120ºF.

Stop use and ask a doctor if irritation occurs.

Keep out of reach of children. If swallowed, get medical help or contact a Poison Control Center right away.

Directions

- to prevent athlete’s foot, wash the feet and dry thoroughly.
- shake can well and spray a thin layer of the product on the feet once or twice daily (morning and/or night).
- supervise children in the use of this product.
- pay special attention to spaces between the toes; wear well-fitting, ventilated shoes, and change shoes and socks at least once daily.

Other information

store between 20º to 25ºC (68º– 77ºF)

Inactive Ingredients

butylated hydroxytoluene, fragrance, hydroxypropyl cellulose, isobutane, kaolin, magnesium stearate, PPG-12-Buteth-16, SD alcohol 40B (9% w/w), zea mays (corn) starch

QUESTIONS

Questions?1-866-360-3266 or visit us at www.lotrimin.com